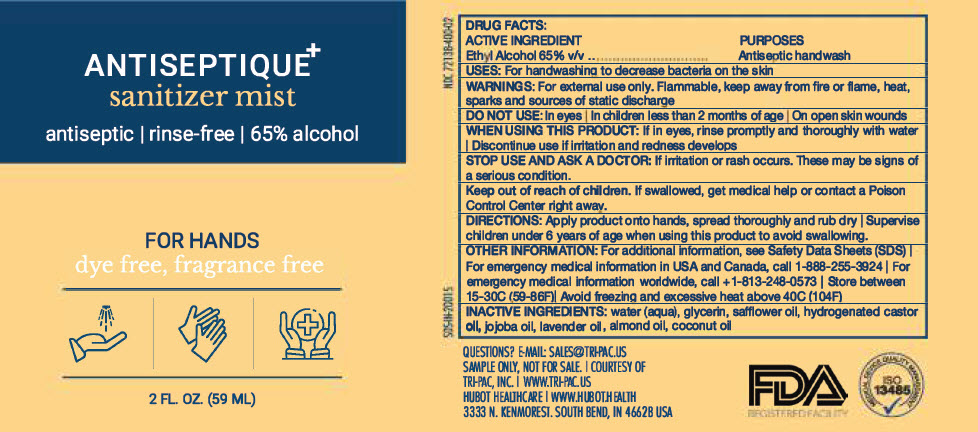 DRUG LABEL: Antiseptique Sanitizer Mist
NDC: 72138-400 | Form: SPRAY
Manufacturer: Hubot Healthcare LLC
Category: otc | Type: HUMAN OTC DRUG LABEL
Date: 20200617

ACTIVE INGREDIENTS: ALCOHOL 65 mL/100 mL
INACTIVE INGREDIENTS: Water; Glycerin; Safflower Oil; Almond Oil; Coconut Oil; Jojoba Oil; Spike Lavender Oil; POLYOXYL 40 HYDROGENATED CASTOR OIL

Antiseptique Sanitizer Mist

Drug Facts

Active ingredient

Ethyl Alcohol 65% v/v

Purposes

Antiseptic handwash

Uses

for handwashing to decrease bacteria on the skin

Warnings

For external use only | Flammable, keep away from fire or flame, heat, sparks, and sources of static discharge

Do not use

In eyes | on children less than 2 months of age | on open skin wounds

When using this product

If in eyes, rinse promptly and thoroughly with water | Discontinue use if irritation and redness develops

Stop use and ask a doctor if skin irritation or redness occurs or persists for more than 72 hours.

Keep out of reach of children. If swallowed, get medical help or contact a Poison Control Center right away.

Directions

Apply product onto hands, spread thoroughly and rub dry | Supervise children under 6 years of age when using this product to avoid swallowing.

Other Information

For additional information, see Safety Data Sheets (SDS) | For emergency medical information in USA and Canada, call 1-888-255-3924 | For emergency medical information worldwide, call 1-813-248-0573| Store between 15-30C (59-86F) | Avoid freexing and excessive heat above 40C (104F)

Inactive Ingredients

water (aqua), glycerin,, safflower oil, hydrogenated castor oil, almond oil, coconut oil, jojoba oil, lavender oil

Questions?

Call 1-855-CLEAN-55 (253-2655)

PRINCIPAL DISPLAY PANEL - 59 ML Bottle Label

ANTISEPTIQUE^+
sanitizer mist

antiseptic | rinse-free | 65% alcohol

FOR HANDS
dye free, fragrance free

2 FL. OZ. (59 ML)